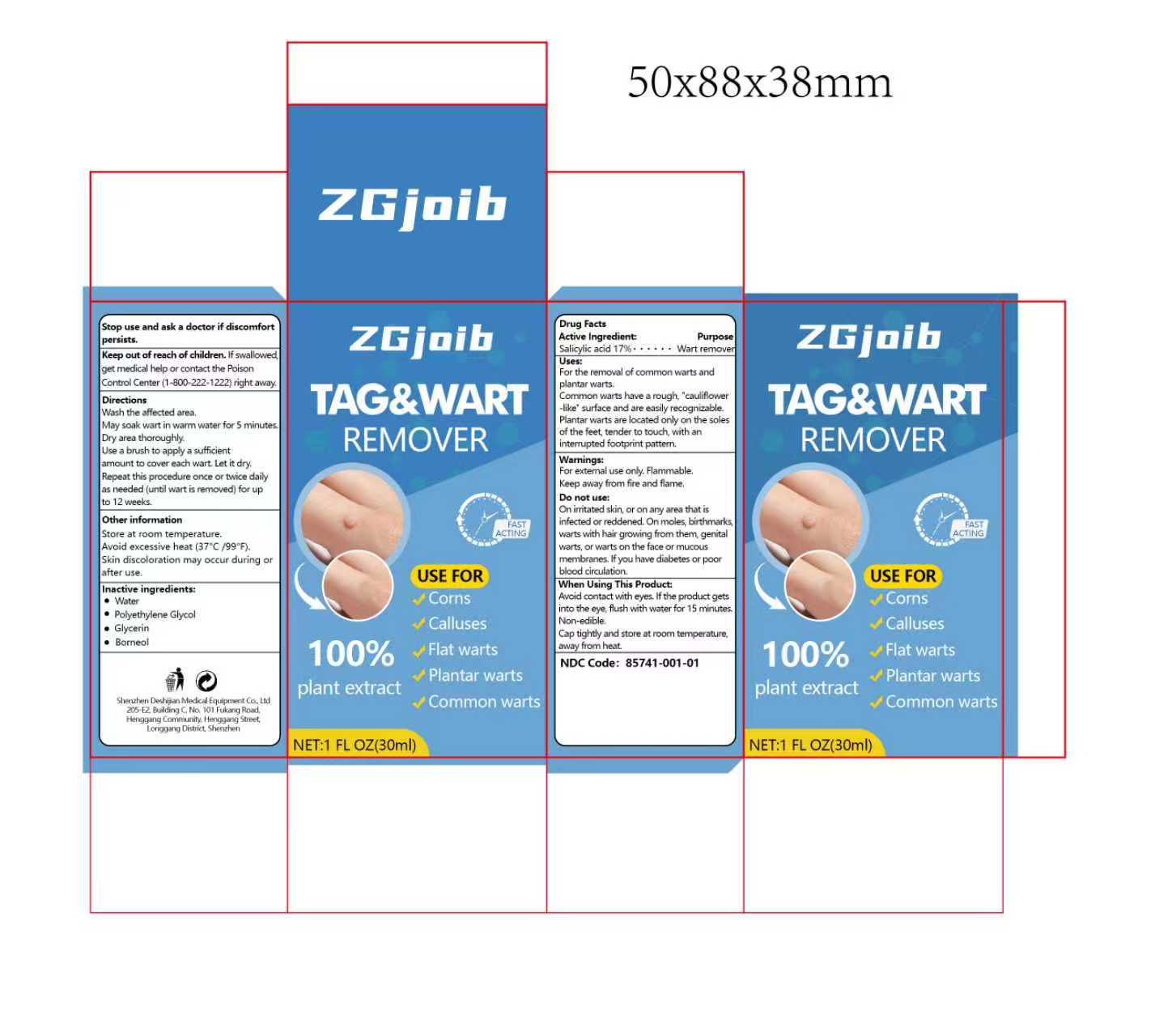 DRUG LABEL: ZGjoib TAG WART REMOVER
NDC: 85741-001 | Form: CREAM
Manufacturer: Shenzhen Deshijian Medical Equipment Co., Ltd
Category: otc | Type: HUMAN OTC DRUG LABEL
Date: 20251202

ACTIVE INGREDIENTS: SALICYLIC ACID 1.7 g/10 mL
INACTIVE INGREDIENTS: WATER; GLYCERIN; POLYETHYLENE GLYCOL, UNSPECIFIED; BORNEOL

85741-001 update

Active ingredient

Active ingredient:Salicylic acid 17%

Inactive ingredient

WaterPolyethylene Glycol- .Glycerin.Borneol.

Keep out of reach of children. lf swallowedget medical help or contact the PoisonControl Center(1-800-222-1222)right away

Purpose section

USE FOR
Corns
Calluses
Flat warts
Plantar warts
Common warts

Warnings

Warnings:For external use only. Flammable.Keep away from fire and flame.

Dosage

Wash the affected area.May soak wart in warm water for 5 minutesDry area thoroughly.Use a brush to apply a sufficientamount to cover each wart. Let it dry.Repeat this procedure once or twice dailyas needed (until wart is removed) for upto 12 weeks.

Do not use:On irritated skin, or on any area that isinfected or reddened. On moles, birthmarkswarts with hair growing from them, genitalwarts, or warts on the face or mucousmembranes. lfyou have diabetes or poorblood circulation.

When Using

When Using This Product:Avoid contact with eyes. lf the product getsinto the eye, flush with water for 15 minutesNon-edible.Cap tightly and store at room temperature.away from heat.

Directions

Wash the affected area.May soak wart in warm water for 5 minutesDry area thoroughly.Use a brush to apply a sufficientamount to cover each wart, Let it dry.Repeat this procedure once or twice dailyas needed (until wart is removed) for upto 12 weeks.

Other information

Other informationStore at room temperature.Avoid excessive heat (37°C /99°F).Skin discoloration may occur during orafter use.